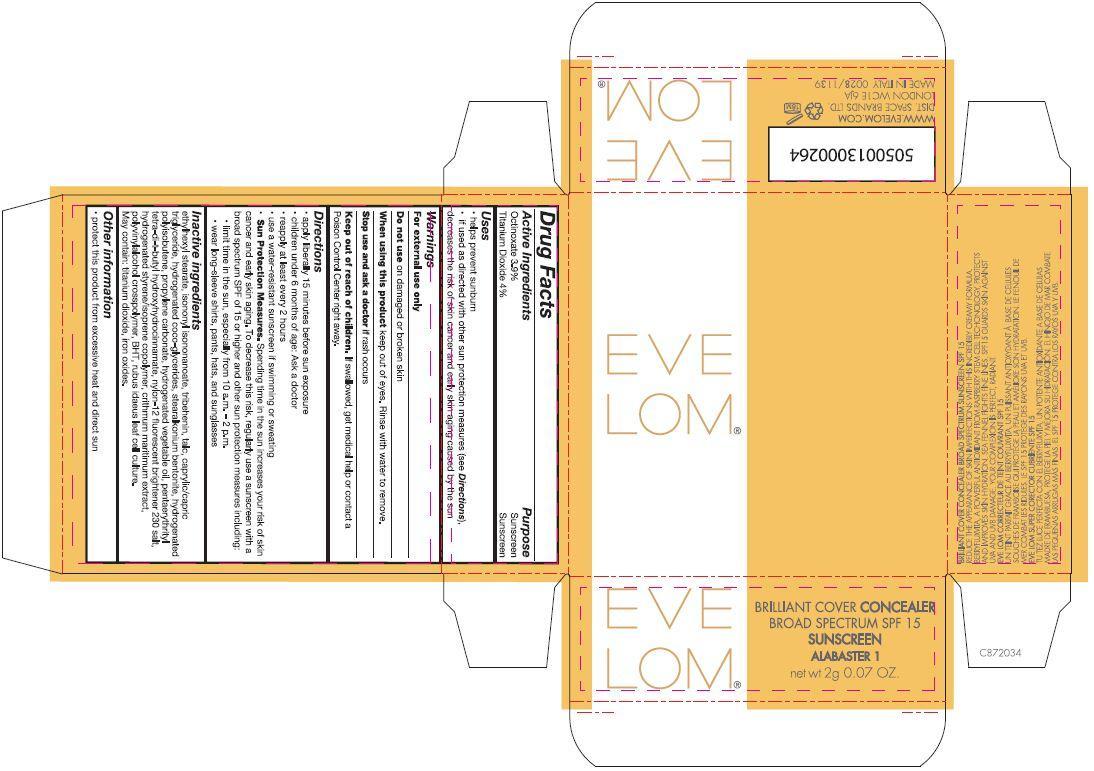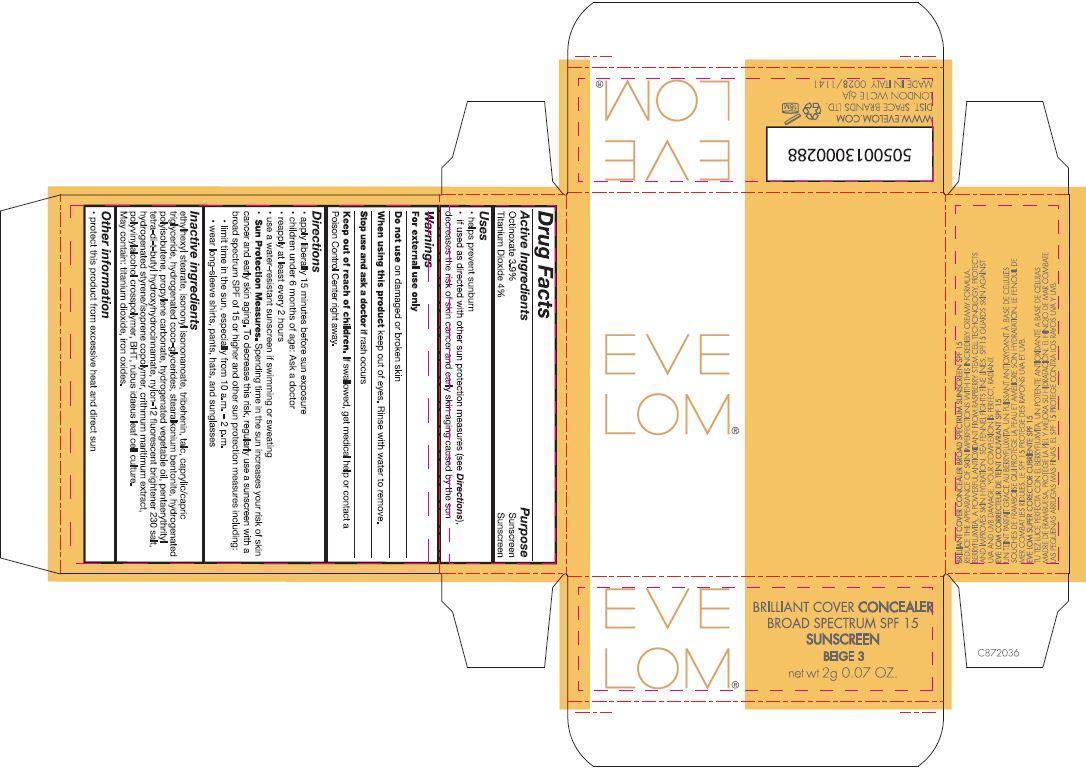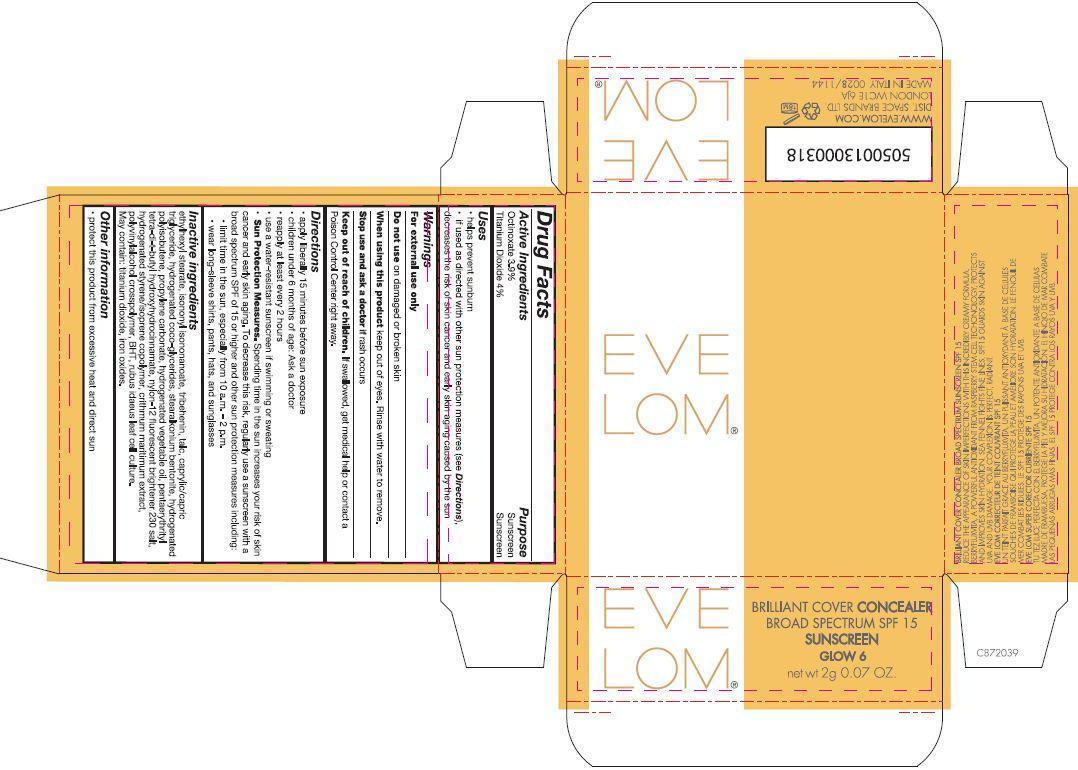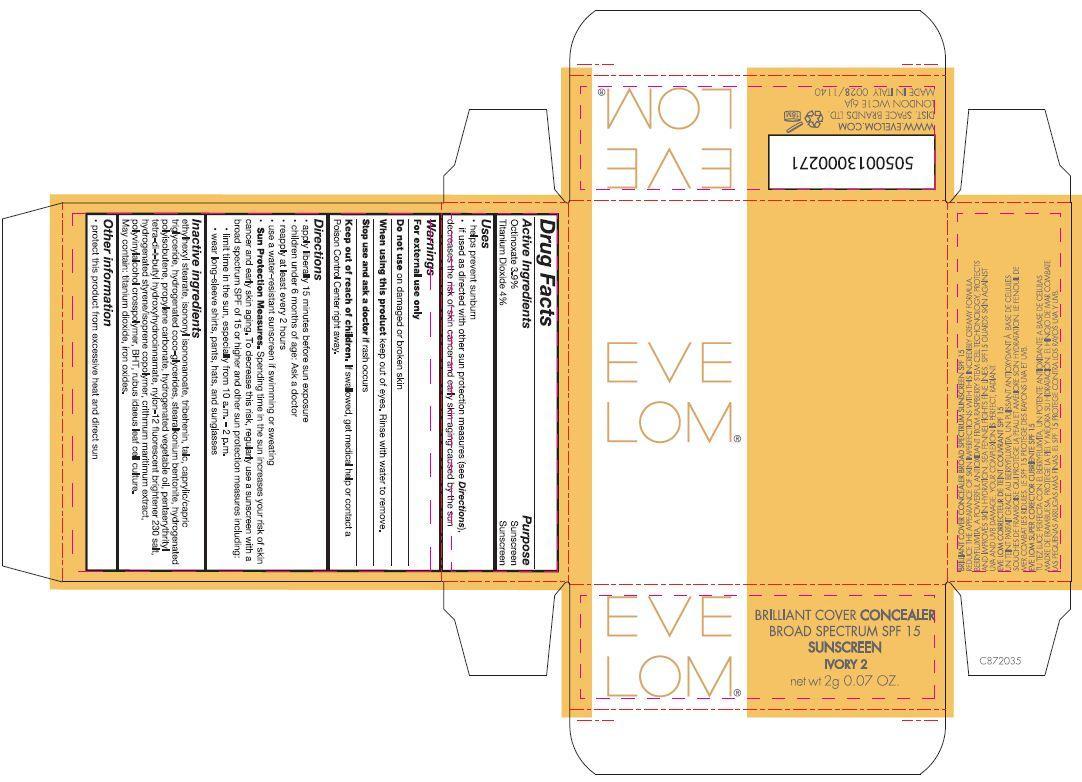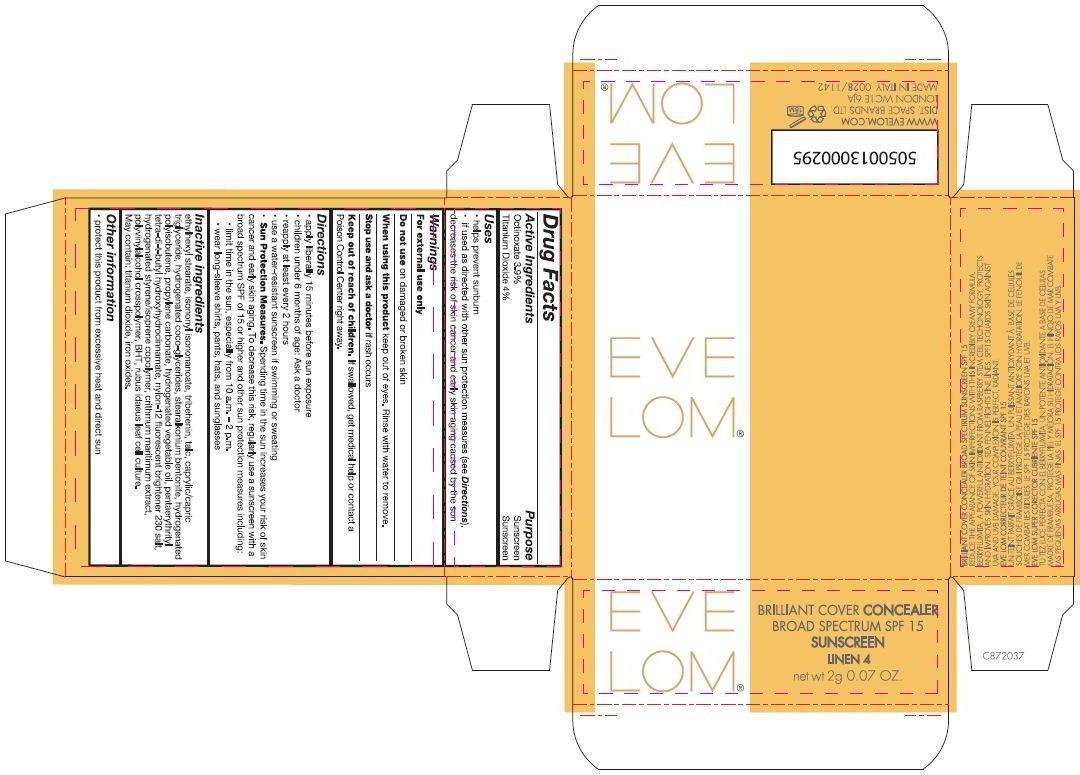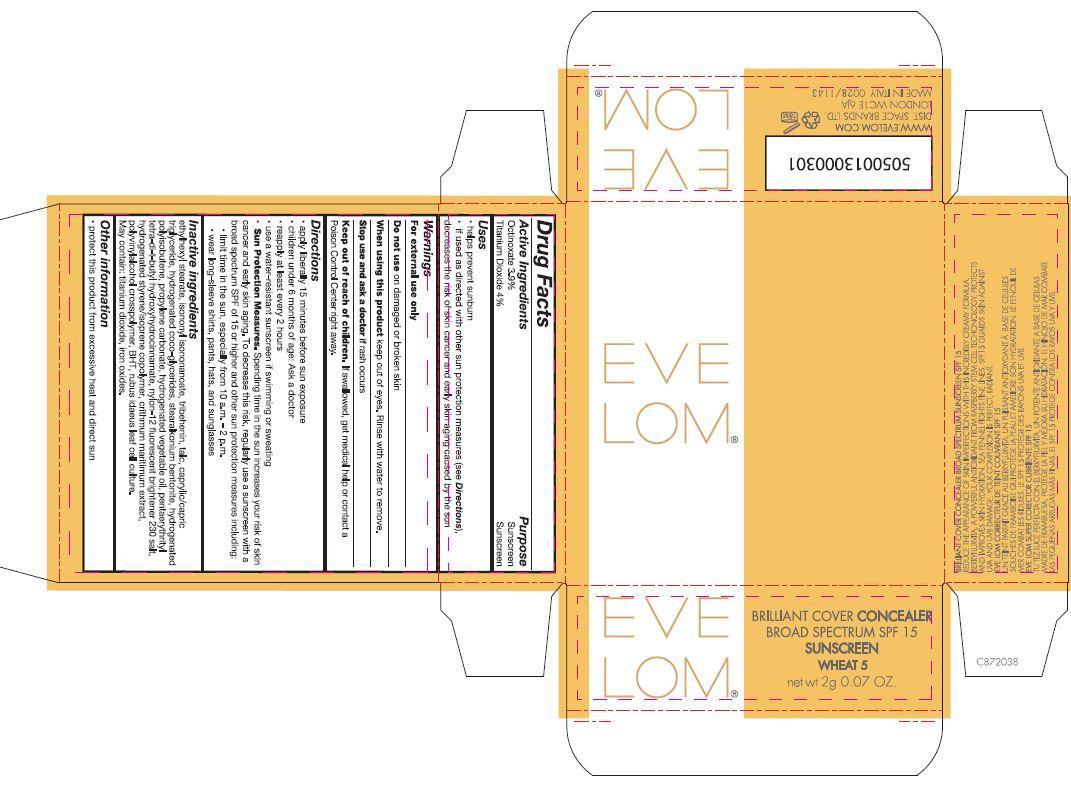 DRUG LABEL: Eve Lom Brilliant Cover Concealer Broad Spectrum SPF 15 Sunscreen
NDC: 61601-1139 | Form: CREAM
Manufacturer: Space Brands Limited
Category: otc | Type: HUMAN OTC DRUG LABEL
Date: 20140320

ACTIVE INGREDIENTS: TITANIUM DIOXIDE 0.08 g/2 g; OCTINOXATE 0.078 g/2 g
INACTIVE INGREDIENTS: ETHYLHEXYL STEARATE; ISONONYL ISONONANOATE; TRIBEHENIN; TALC; MEDIUM-CHAIN TRIGLYCERIDES; HYDROGENATED COCO-GLYCERIDES; FERRIC OXIDE YELLOW; HYDROGENATED POLYBUTENE (1300 MW); FERRIC OXIDE RED; PROPYLENE CARBONATE; FERROSOFERRIC OXIDE; PENTAERYTHRITOL TETRAKIS(3-(3,5-DI-TERT-BUTYL-4-HYDROXYPHENYL)PROPIONATE); CRITHMUM MARITIMUM; BUTYLATED HYDROXYTOLUENE

Eve Lom® Brilliant Cover Concealer Broad Spectrum SPF 15 Sunscreen

Drug Facts

ACTIVE INGREDIENT

Active Ingredients Purpose

Octinoxate 3.9% Sunscreen

Titanium Dioxide 4% Sunscreen

Uses

- helps prevent sunburn
- if used as directed with other sun protection measure (see Directions), decreases the risk of skin cancer and early skin aging caused by the sun

Warnings

For external use only

Do not use on damages or broken skin

When using this product keep out of eyes. Rinse with water to remove.

Stop use and ask a doctor if rash occurs

Keep out of reach of children.If swallowed, get medical help or contact a Poison Control Center right away.

DOSAGE AND ADMINISTRATION

- apply liberally 15 minutes before sun exposure
- children under 6 months of age: Ask a doctor
- reapply at least every 2 hours
- use a water-resistant sunscreen if swimming or sweating
- Sun Protection Measures. Spending time in the sun increases your risk of skin cancer and early skin aging. To decrease this risk, regularly use a sunscreen with a broad spectrum SPF of 15 or higher and other sun protection measures including:
  - limit time in the sun, especially from 10 a.m. – 2 p.m.
  - wear long-sleeve shirts, pants, hats, and sunglasses

Inactive ingredients

ethylhexyl stearate, isononyl isononanoate, tribehenin, talc, caprylic/capric triglyceride, hydrogenated coco-glycerides, stearalkonium bentonite, hydrogenated polyisobutene, propylene carbonate, hydrogenated vegetable oil, pentaerythrityl tetra-di-t-butyl hydroxyhydrocinnamate, nylon-12 fluorescent brightener 230 salt, hydrogenated styrene/isoprene copolymer, crithmum maritimum extract, polyvinylalcohol crosspolymer, BHT, rubus idaeus leaf cell culture.

May contain: titanium dioxide, iron oxides.

Other information

- protect this product from excessive heat and direct sun

PRINCIPAL DISPLAY PANEL - 2 g Container Carton - Alabaster

EVE LOM®

BRILLIANT COVER CONCEALER

BROAD SPECTRUM SPF 15

SUNSCREEN

ALABASTER 1

net wt 2g 0.07 OZ

PRINCIPAL DISPLAY PANEL - 2 g Container Carton - Ivory

EVE LOM®

BRILLIANT COVER CONCEALER

BROAD SPECTRUM SPF 15

SUNSCREEN

IVORY 2

net wt 2g 0.07 OZ

PRINCIPAL DISPLAY PANEL - 2 g Container Carton - Linen

EVE LOM®

BRILLIANT COVER CONCEALER

BROAD SPECTRUM SPF 15

SUNSCREEN

LINEN 4

net wt 2g 0.07 OZ

PRINCIPAL DISPLAY PANEL - 2 g Container Carton - Beige

EVE LOM®

BRILLIANT COVER CONCEALER

BROAD SPECTRUM SPF 15

SUNSCREEN

BEIGE 3

net wt 2g 0.07 OZ

PRINCIPAL DISPLAY PANEL - 2 g Container Carton - Wheat

EVE LOM®

BRILLIANT COVER CONCEALER

BROAD SPECTRUM SPF 15

SUNSCREEN

WHEAT 5

net wt 2g 0.07 OZ

PRINCIPAL DISPLAY PANEL - 2 g Container Carton - Glow

EVE LOM®

BRILLIANT COVER CONCEALER

BROAD SPECTRUM SPF 15

SUNSCREEN

GLOW 6

net wt 2g 0.07 OZ